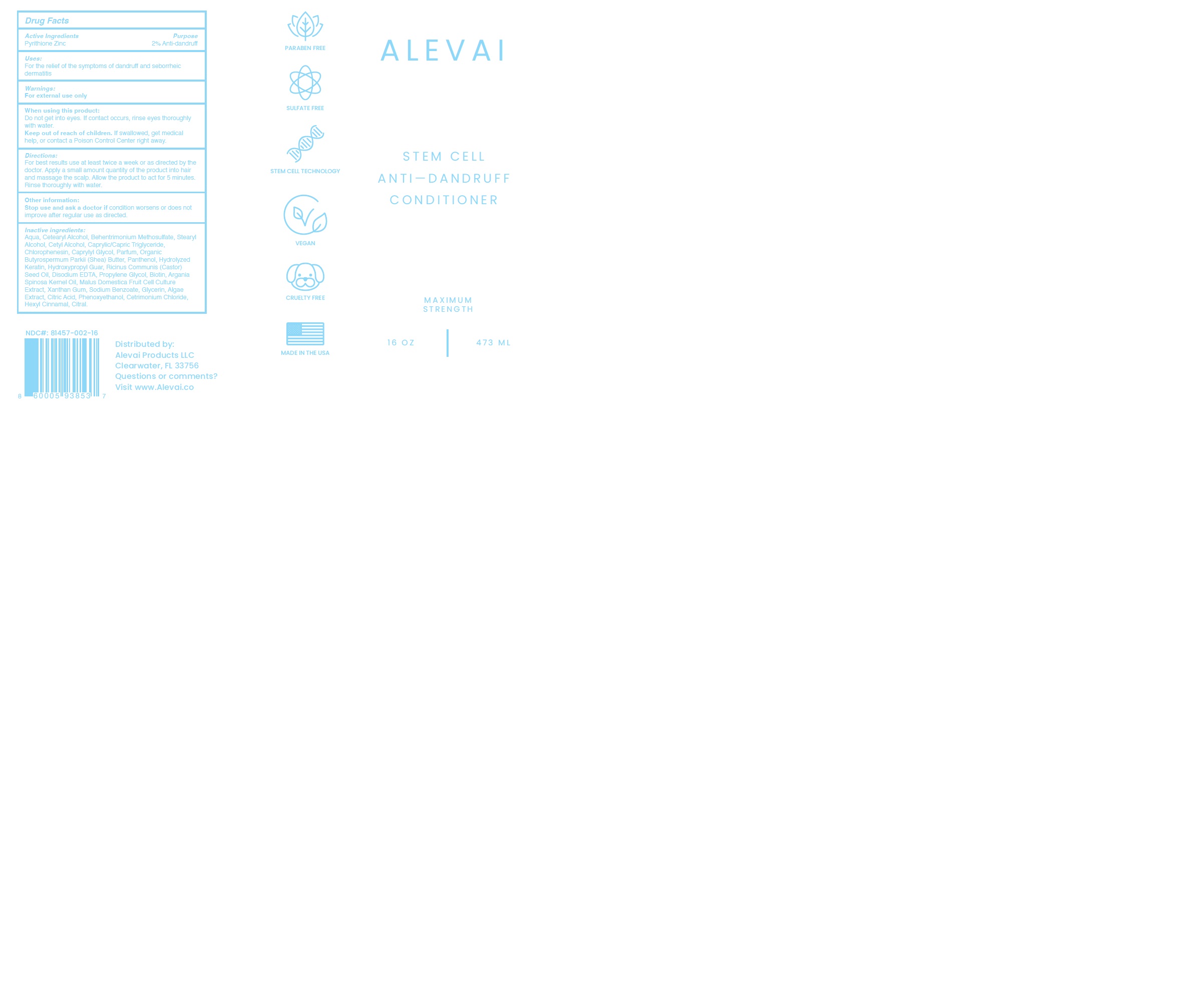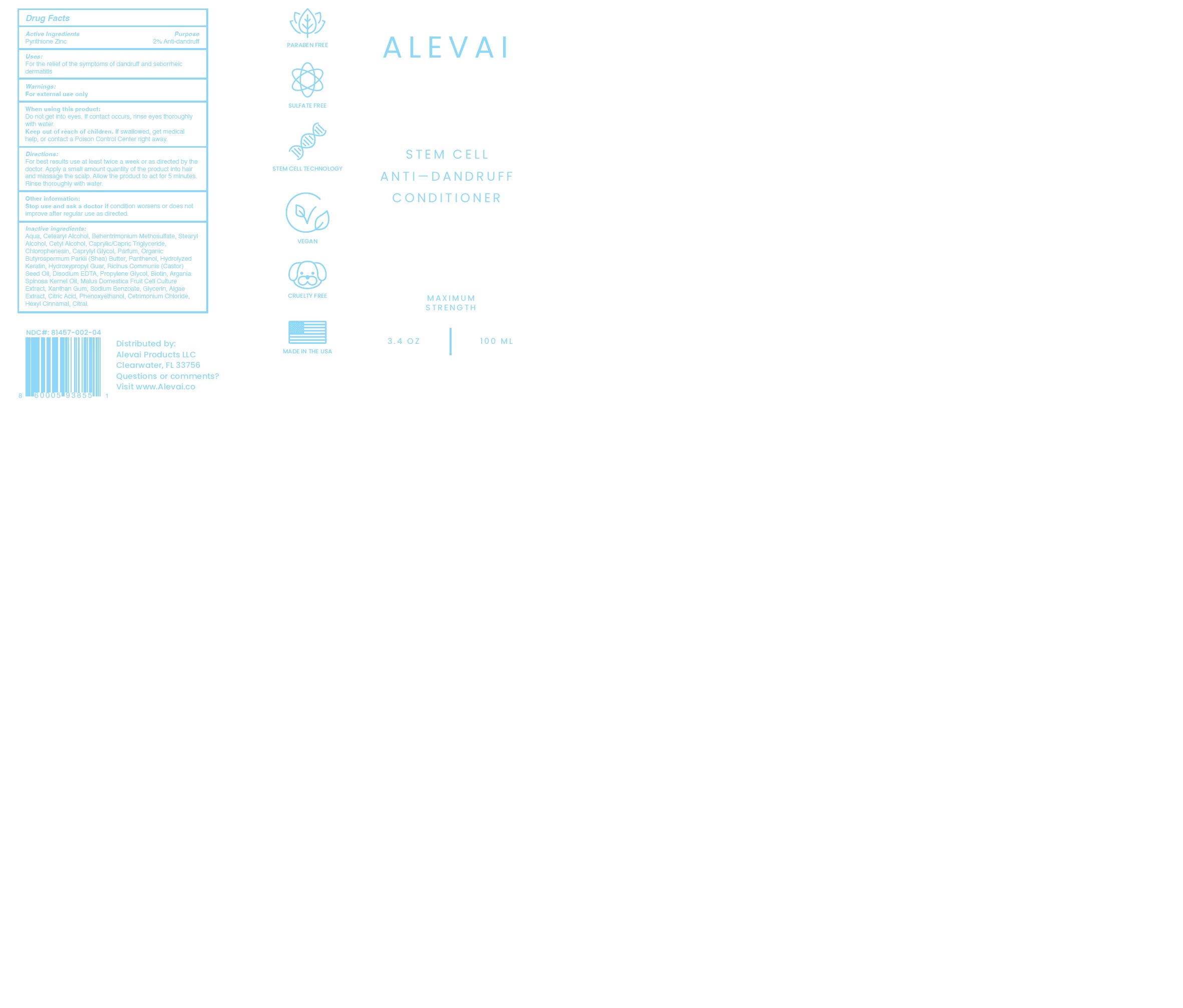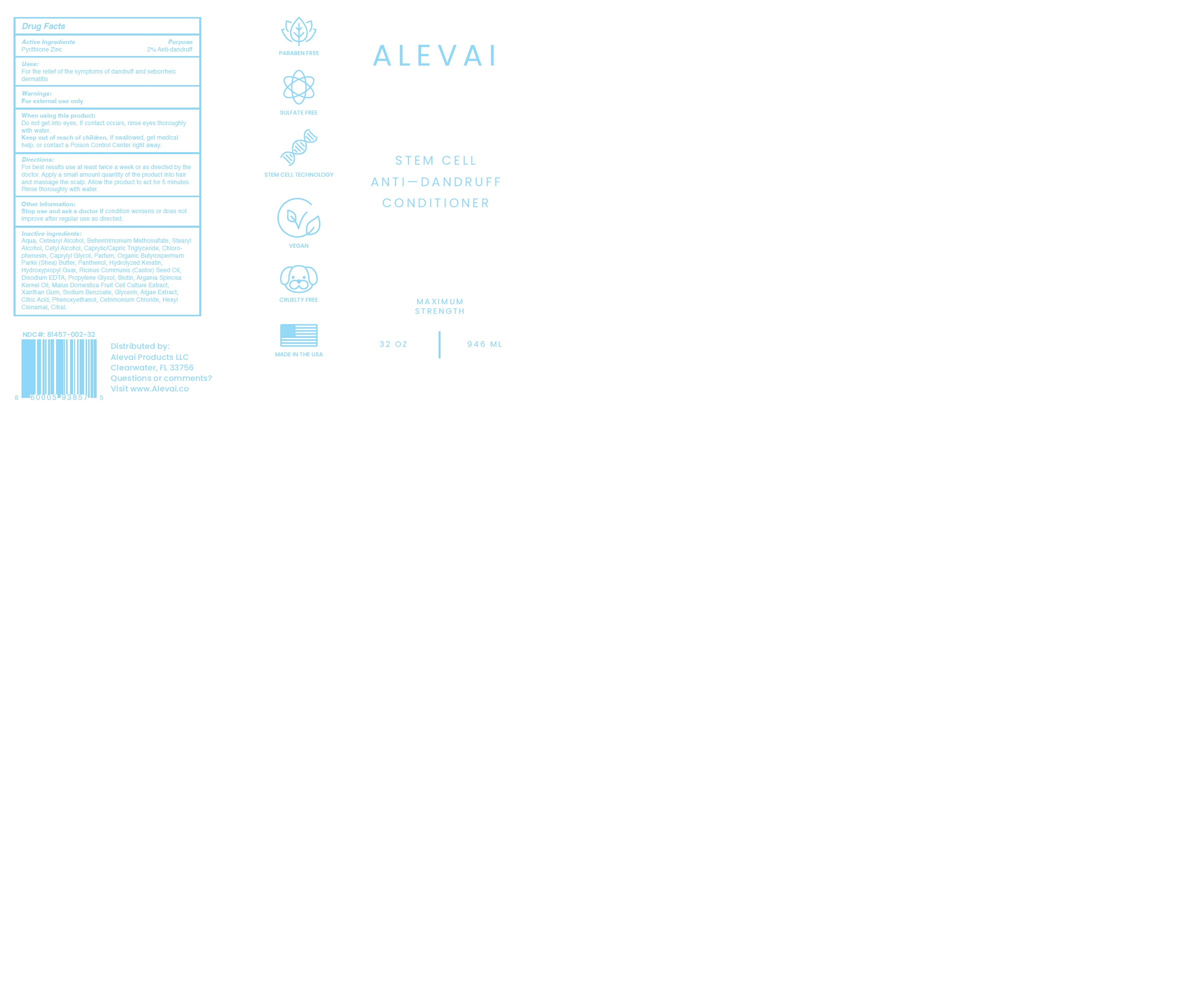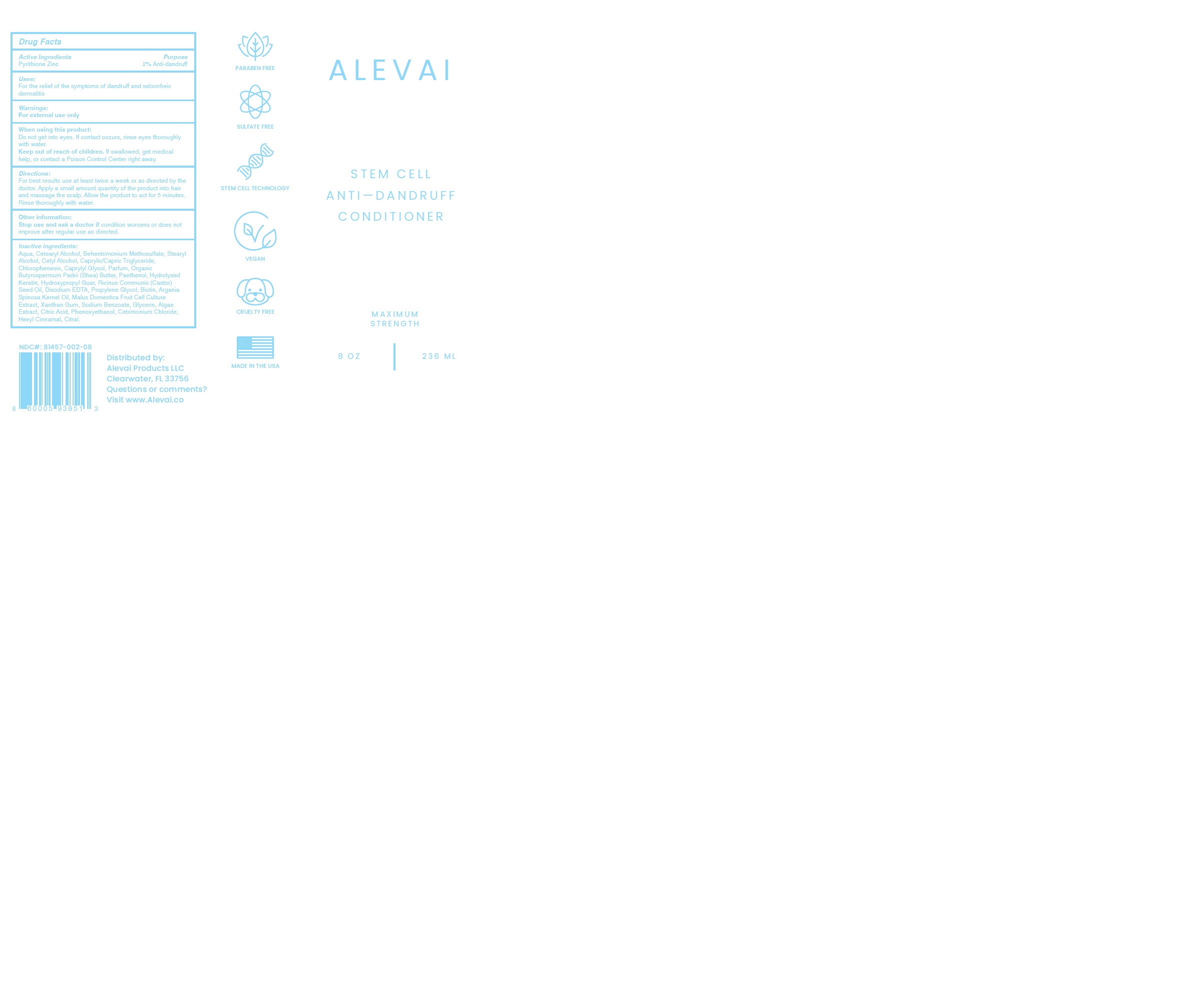 DRUG LABEL: ALEVAI – STEM CELL ANTI-DANDRUFF CONDITIONER
NDC: 81457-002 | Form: LOTION
Manufacturer: ALEVAI PRODUCTS LLC
Category: otc | Type: HUMAN OTC DRUG LABEL
Date: 20220714

ACTIVE INGREDIENTS: PYRITHIONE ZINC 2.1 g/100 mL
INACTIVE INGREDIENTS: CETOSTEARYL ALCOHOL; .ALPHA.-HEXYLCINNAMALDEHYDE; SHEA BUTTER; PROPYLENE GLYCOL; STEARYL ALCOHOL; WATER; BEHENTRIMONIUM METHOSULFATE; GLYCERIN; PHENOXYETHANOL; HYDROXYPROPYL GUAR (2500-4500 MPA.S AT 1%); SODIUM BENZOATE; CETYL ALCOHOL; RICINUS COMMUNIS SEED; BIOTIN; ARGANIA SPINOSA WHOLE; MALUS DOMESTICA WHOLE; PANTHENOL; CETRIMONIUM CHLORIDE; CAPRYLYL GLYCOL; XANTHAN GUM; CHLORPHENESIN; EDETATE DISODIUM; ANHYDROUS CITRIC ACID; MEDIUM-CHAIN TRIGLYCERIDES

81457-002-04
81457-002-08
81457-002-16
81457-002-32

ACTIVE INGREDIENT

Pyrithione Zinc………………………………………………………………………………………. 2% Anti-dandruff

PURPOSE

For the relief of the symptoms of dandruff and seborrheic dermatitis

INDICATIONS AND USAGE

Do not get into eyes. If contact occurs rinse eyes thoroughly with water.

WARNINGS

For external use only.

WHEN USING

Do not get into eyes. If contact occurs rinse eyes thoroughly with water.

KEEP OUT OF REACH OF CHILDREN

KEEP out of the reach of children. If swallowed, get medical help, or contact a Poison Control Center right away.

DOSAGE AND ADMINISTRATION

For best results use at least twice a week or as directed by the doctor.

Apply a small amount quantity of the product into hair and massage the scalp.

Allow the product to act for 5 minutes.

Rinse thoroughly with water.

Stop use and ask a doctor if conditions worsen or does not improve after regular use as directed.

INACTIVE INGREDIENT

Aqua, Cetearyl Alcohol, Behentrimonium Methosulfate, Stearyl Alcohol, Cetyl Alcohol, Caprylic/Capric Triglyceride, Chlorophenesin, Caprylyl Glycol, Parfum, Organic Butyrospermum Parkii (Shea) Butter, Panthenol, Hydrolyzed Keratin, Hydroxypropyl Guar, Ricinus Communis (Castor) Seed Oil, Disodium EDTA, Propylene Glycol, Biotin, Argania Spinosa Kernel Oil, Malus Domestica Fruit Cell Culture Extract, Xanthan Gum, Sodium Benzoate, Glycerin, Algae Extract, Citric Acid, Phenoxyethanol, Cetrimonium Chloride, Hexyl Cinnamal, Citral.